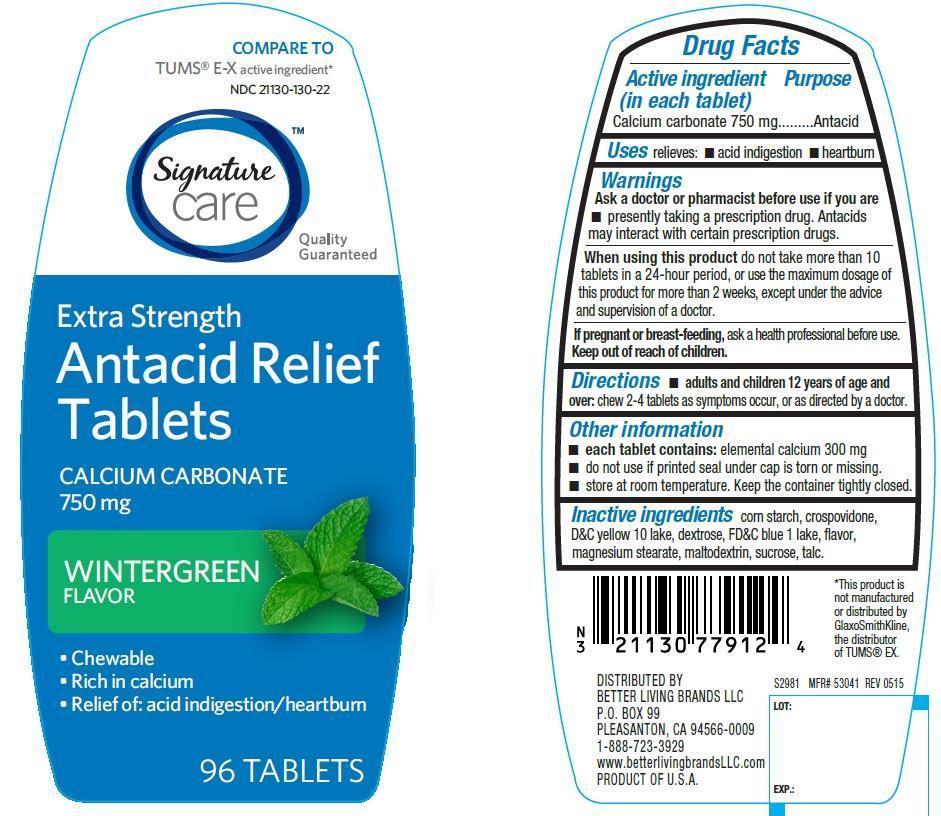 DRUG LABEL: Antacid Relief Extra Strength
NDC: 21130-130 | Form: TABLET, CHEWABLE
Manufacturer: Safeway
Category: otc | Type: HUMAN OTC DRUG LABEL
Date: 20220112

ACTIVE INGREDIENTS: CALCIUM CARBONATE 750 mg/1 1
INACTIVE INGREDIENTS: STARCH, CORN; CROSPOVIDONE; D&C YELLOW NO. 10; DEXTROSE, UNSPECIFIED FORM; FD&C BLUE NO. 1; MAGNESIUM STEARATE; MALTODEXTRIN; SUCROSE; TALC

Extra strength Antacid Relief Wintergreen Tablets

Active ingredient (in each tablet)

Calcium carbonate 750 mg

Purpose

Antacid

Uses

relieves

- acid indigestion
- heartburn

Warnings

Ask a doctor or pharmacist before use if you are

- presently taking a prescription drug. Antacids may interact with certain prescriptiom drugs.

When using this product

do not take more than 10 tablets in a 24-hour period, or use the maximum dosage of this product for more than 2 weeks, except under the advice and supervision of a doctor.

If pregnant or breast-feeding, ask a health professional before use.

Keep out of reach of children

Directions

- adults and children 12 years of age and over: chew 2-4 tablets as symptoms occur, or as directed by a doctor

Other information

- each tablet contains: elemental calcium 300 mg
- do not use if seal under cap is torn or missing
- store at room temperature. keep the container tightly closed.

Inactive ingredients

corn starch, crospovidone, D&C Yellow 10 lake, dextrose, FD&C blue 1 lake, flavor, magnesium stearate, maltodextrin, sucrose, talc

Principal Display Panel

COMPARE TO Tums® E-X active ingredient*

NDC 21130-130-22

Signature Care

Extra Strength Antacid Relief Tablets

CALCIUM CARBONATE 750 mg

WINTERGREEN FLAVOR

- Chewable
- Rich in calcium
- Relief of: acid indigestion/heartburn

96 tablets